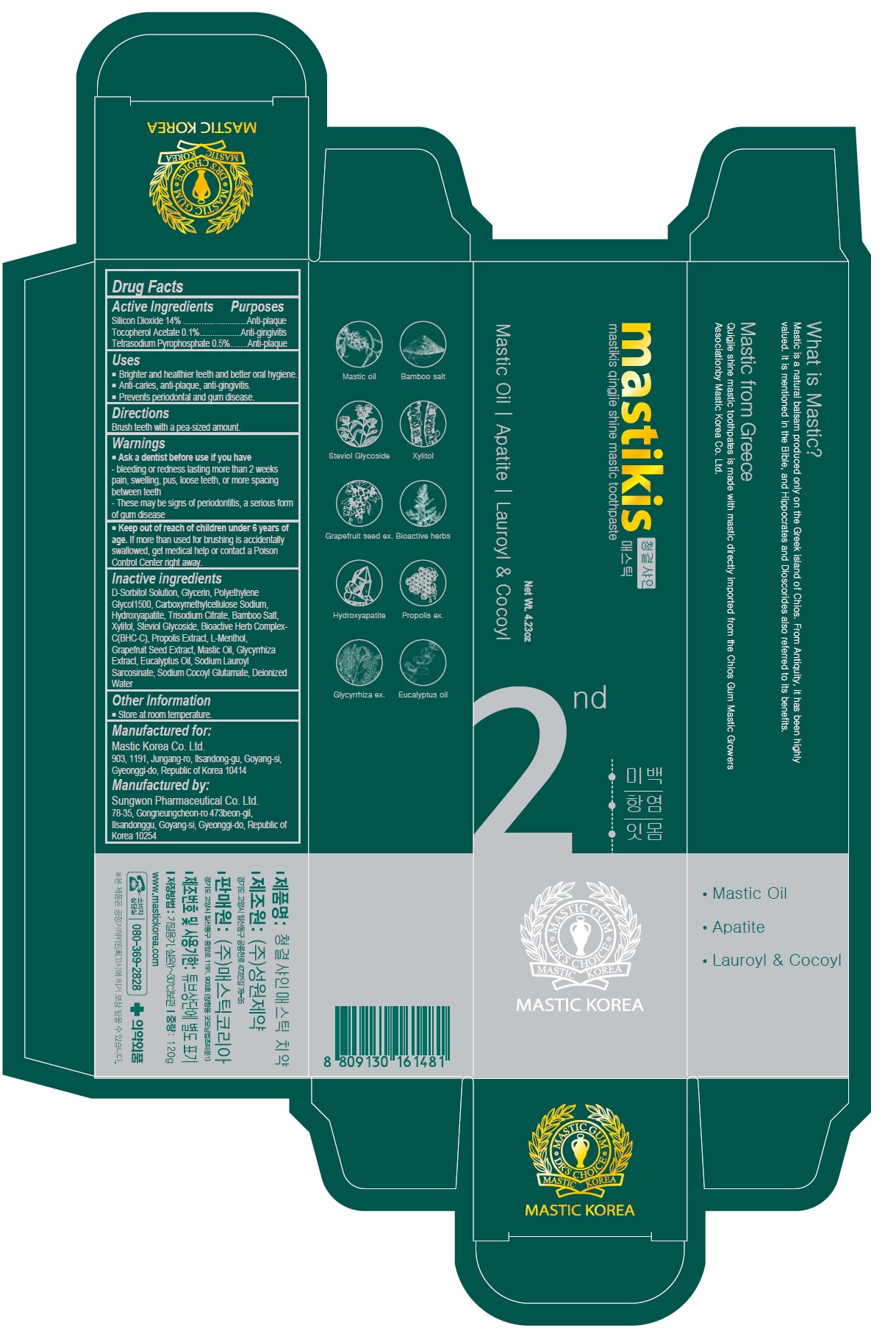 DRUG LABEL: Mastikis Qingjie Shine Mastic
NDC: 79814-004 | Form: PASTE, DENTIFRICE
Manufacturer: Mastic Korea.Co.Ltd
Category: otc | Type: HUMAN OTC DRUG LABEL
Date: 20200914

ACTIVE INGREDIENTS: SILICON DIOXIDE 14 g/100 g; .ALPHA.-TOCOPHEROL ACETATE 0.1 g/100 g; SODIUM PYROPHOSPHATE 0.5 g/100 g
INACTIVE INGREDIENTS: SORBITOL; GLYCERIN; POLYETHYLENE GLYCOL 1600; CARBOXYMETHYLCELLULOSE SODIUM, UNSPECIFIED; TRIBASIC CALCIUM PHOSPHATE; SODIUM CITRATE, UNSPECIFIED FORM; XYLITOL; STEVIOSIDE; PROPOLIS WAX; LEVOMENTHOL; CITRUS PARADISI SEED; LICORICE; EUCALYPTUS OIL; SODIUM LAUROYL SARCOSINATE; SODIUM COCOYL GLUTAMATE; WATER

79814-004_Mastikis Qingjie Shine Mastic Toothpaste

ACTIVE INGREDIENT

Silicon Dioxide 14%

Tocopherel Acetate 0.1%

Tetrasodium Pyrophosphate 0.5%

INACTIVE INGREDIENT

D-Sorbitol Solution, Glycerin, Polyethylene Glycol1500, Carboxymethylcellulose Sodium, Hydroxyapatite, Trisodium Citrate, Bamboo salt, Xylitol, Steviol Glycoside, Bioactive Herb Complex-C(BHC-C), Propolis Extract, L-Menthol, Grapefruit Seed Extract, Mastic Oil, Glycyrrhiza Extract, Eucalyptus Oil, Sodium Lauroyl Sarcosinate, Sodium Cocoyl Glutamate, Deionized Water

Keep out of Reach of Children.

PURPOSE

Anti-gingivitis

Anti-plaque

WARNINGS

Ask a dentist before use if you have

- bleeding or redness lasting more than 2 weeks pain, swelling, pus, losse teeth, or more spacing between teeth

- These may be signs of periodontitis, a serious form of gum disease

INDICATIONS AND USAGE

- Brighter and healthier teeth and better oral hygiene

- Anti-caries, anti-plaque, anti--gingivitis

- Prevents periodontal and gum disease

DOSAGE AND ADMINISTRATION

Brush teeth with a pea-sized amount